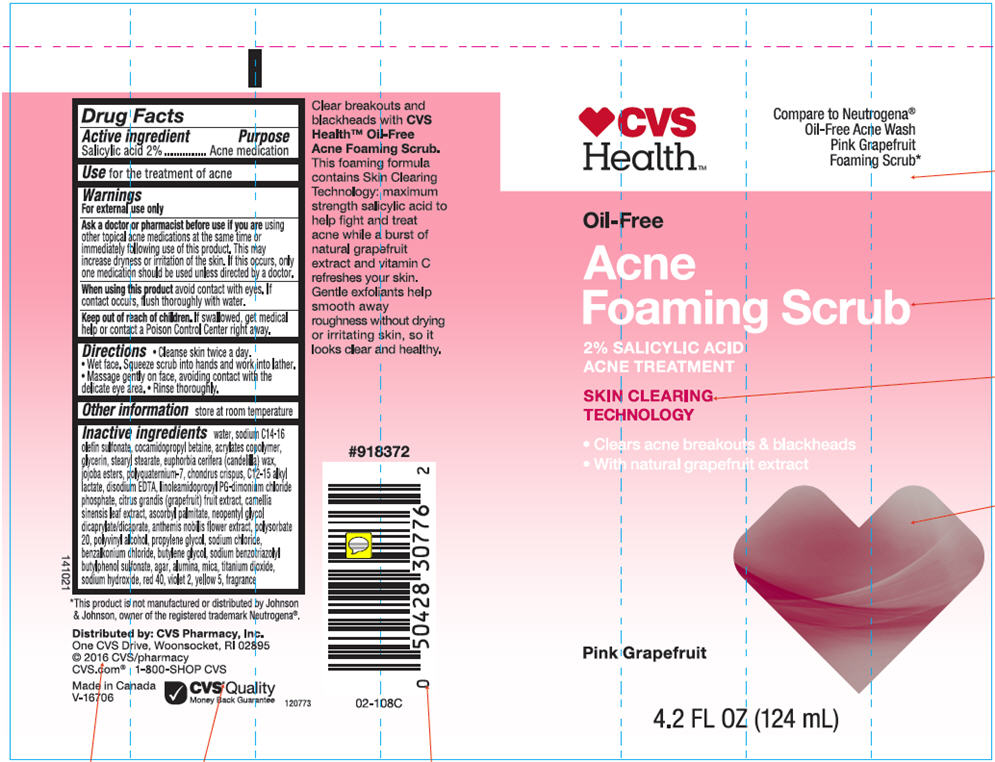 DRUG LABEL: CVS Oil Free Acne Foaming Scrub-Pink Grapefruit 
NDC: 69842-603 | Form: LOTION
Manufacturer: CVS Health
Category: otc | Type: HUMAN OTC DRUG LABEL
Date: 20220126

ACTIVE INGREDIENTS: Salicylic Acid 20 mg/1 mL
INACTIVE INGREDIENTS: Water; Sodium C14-16 Olefin Sulfonate; Cocamidopropyl Betaine; Polyquaternium-7 (70/30 Acrylamide/dadmac; 1600000 MW); Glycerin; Stearyl Stearate; Candelilla Wax; Hydrolyzed Jojoba Esters (Acid Form); Chondrus Crispus; C12-15 Alkyl Lactate; Edetate Disodium; Linoleamidopropyl Propylene Glycol-Dimonium Chloride Phosphate; Pummelo; Green Tea Leaf; Ascorbyl Palmitate; Neopentyl Glycol Dicaprylate/Dicaprate; Chamaemelum Nobile Flower; Polysorbate 20; Polyvinyl Alcohol (100000 MW); Propylene Glycol; Sodium Chloride; Benzalkonium Chloride; Butylene Glycol; Sodium Benzotriazolyl Butylphenol Sulfonate; Agar, Unspecified; Aluminum Oxide; Mica; Titanium Dioxide; Sodium Hydroxide; FD&C Red No. 40; D&C Violet No. 2; FD&C Yellow No. 5

CVS Oil Free Acne Foaming Scrub-Pink Grapefruit
Acne Medication

Active ingredients

Salicylic Acid 2.0%

Purpose

Acne Medication

Use

For the treatment of acne

Warnings

For external use only

Ask a doctor or pharmacist before use if you are using other topical acne medications at the same time or immediately following use of this product. This may increase dryness or irritation of the skin. If this occurs, only one medication should be used unless directed by a doctor.

When using this product avoid contact with eyes. If contact occurs, flush thoroughly with water.

Keep out of reach of children. If swallowed, get medical help or contact a Poison Control Center right away.

Directions

♦ Cleanse skin twice a day.
♦ Wet face. Squeeze scrub into hands and work into lather.
♦ Massage gently on face, avoiding contact with the delicate eye area.
♦ Rinse well.

Other information

store at room temperature

Inactive ingredients

Water, Sodium C14-16 Olefin Sulfonate, Cocamidopropyl Betaine, Acrylates Copolymer, Glycerin, Stearyl Stearate, Euphorbia Cerifera (Candelilla) Wax, Jojoba Esters, Polyquaternium-7, Chondrus Crispus, C12-15Alkyl Lactate, Disodium EDTA, Linoleamidopropyl PG-diamonium Chloride Phosphate, Citrus Grandis (Grapefruit) Fruit Extract, Camellia Sinensis Leaf Extract, Ascorbyl Palmitate, Neopentyl Glycol Dicaprilate/Dicaprate, Anthemis Nobilis Flower Extract, Polysorbate 20, Polyvinyl Alcohol, Propylene Glycol, Sodium Chloride, Benzalkonium Chloride, Butylene Glycol, Sodium Benzotriazolyl Butylphenol Sulfonate, Agar, Alumina, Mica, Titanium Dioxide, Sodium Hydroxide, Red 40, Violet 2, Yellow 5, Fragrance.

Distributed by: CVS Pharmacy, Inc.
One CVS Drive, Woonsocket, RI 02895

PRINCIPAL DISPLAY PANEL - 124 mL Tube Label

♥CVS
Health™

Compare to Neutrogena®
Oil-Free Acne Wash
Pink Grapefruit
Foaming Scrub*

Oil-Free

Acne
Foaming Scrub

2% SALICYLIC ACID
ACNE TREATMENT

SKIN CLEARING
TECHNOLOGY

- Clears acne breakouts & blackheads
- With natural grapefruit extract

Pink Grapefruit

4.2 FL OZ (124 mL)